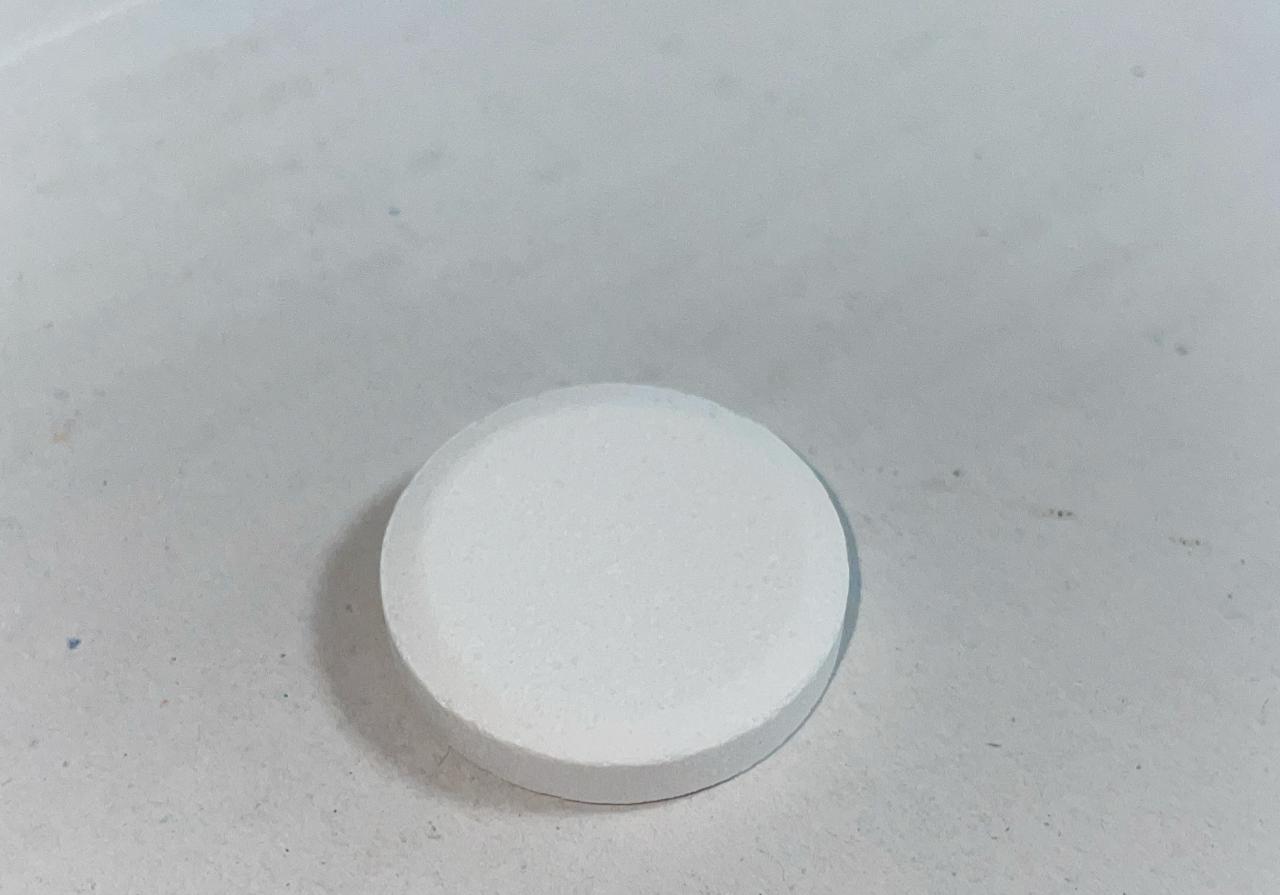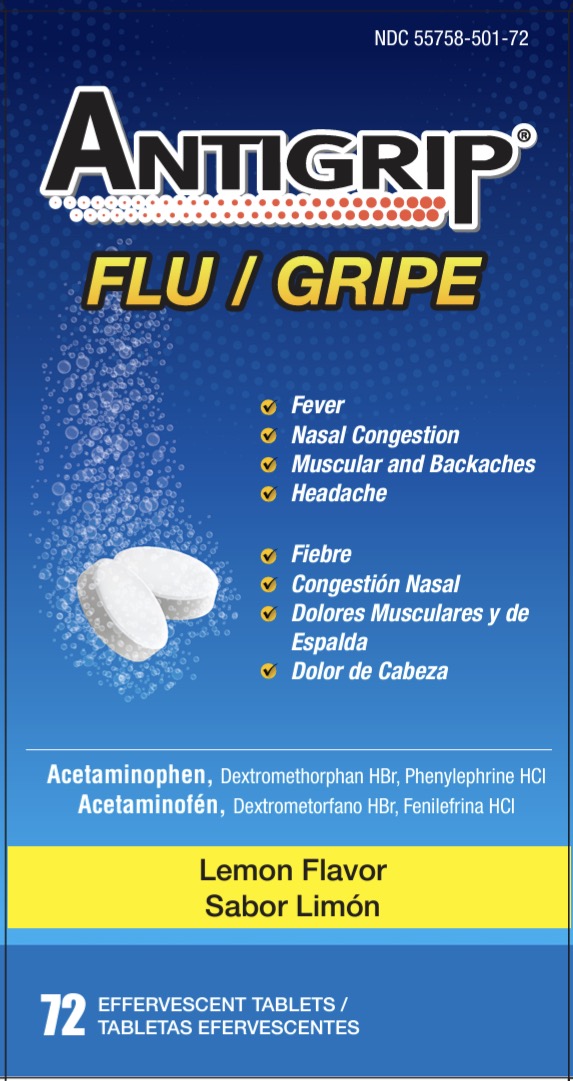 DRUG LABEL: Antigrip
NDC: 55758-501 | Form: TABLET, EFFERVESCENT
Manufacturer: Pharmadel LLC
Category: otc | Type: HUMAN OTC DRUG LABEL
Date: 20241029

ACTIVE INGREDIENTS: PHENYLEPHRINE HYDROCHLORIDE 5 mg/1 1; ACETAMINOPHEN 325 mg/1 1; DEXTROMETHORPHAN HYDROBROMIDE 10 mg/1 1
INACTIVE INGREDIENTS: WATER; ACESULFAME POTASSIUM; ANHYDROUS CITRIC ACID; POLYSORBATE 80; POVIDONE K30; SODIUM BENZOATE; SUCRALOSE; SODIUM BICARBONATE; DIMETHICONE; SILICON DIOXIDE

Antigrip Flu Blue Effervescent (V)

Active ingredients & Purposes

PURPOSE

Active ingredients (in each tablet) | Purposes
Acetaminophen 325 mg................... | Pain reliever/ fever reducer
Dextromethorphan HBr 10 mg ........... | Cough suppressant
Phenylephrine HCl 5 mg ..................... | Nasal decongestant

Uses

For the temporary relief of symptoms due to the common cold/ flu:

- cough due to minor bronchial irritation
- nasal congestion
- minor aches and pains
- headache
- and temporarily reduces fever

Warnings

Liver Warning: This product contains acetaminophen. Severe liver damage may occur if you take

- more than 12 tablets in 24 hours, which is the maximum daily amount for this product
- with other drugs containing acetaminophen
- 3 or more alcoholic drinks every day while using this product

Allergy alert: Acetaminophen may cause severe skin reactions. Symptoms may include:

- skin reddening
- blisters
- rash.

If a skin reaction occurs, stop use and seek medical help right away.

Do not use

- with any other drug containing acetaminophen (prescription or nonprescription). If you are not sure whether a drug contains acetaminophen, ask a doctor or pharmacist.
- if you are now taking a prescription monoamine oxidase inhibitor (MAOI) (certain drugs for depression, psychiatric, or emotional

conditions, or Parkinson’s disease), or for 2 weeks after stopping the MAOI drug. If you do not know if your prescription drug contains an MAOI, ask your doctor or pharmacist before taking this product

Ask a doctor before use if you have

- liver disease
- heart disease
- high blood pressure
- thyroid disease
- diabetes
- difficulty in urination due to enlargement of the prostate gland
- a persistent or chronic cough such as occurs with smoking, asthma, or emphysema, or if cough is accompanied by excessive phlegm (mucus)

Ask a doctor or pharmacist before use if you are

- taking the blood thinning drug warfarin

When using this product

- do not exceed the recommended dosage

Stop use and ask a doctor if

- nervousness, dizziness, or sleeplessness occurs
- pain, cough, or nasal congestion persists for more than 7 days
- fever gets worse or lasts more than 3 days
- redness or swelling is present
- new symptoms occur
- cough comes back or occurs with a rash or headache that lasts. These could be signs of a serious condition.

If pregnant or breastfeeding,

ask a health professional before use.

Keep out of reach of children.

In case of an accidental overdose, get medical help or contact a Poison Control Center right away. Prompt medical attention is critical for adults as well as for children even if you do not notice any signs or symptoms.

Directions

■ adults and children 12 years of age and older: take two (2) tablets fully dissolved in a 4 oz glass of water every 4 hours. Do not exceed 12 tablets in 24 hours or as directed by a doctor.

■ children under 12 years of age: do not use

Other information

- each tablet contains: potassium 10mg, sodium 274mg
- store below 77° F(25° C) and in a dry place

Inactive Ingredients

acesulfame potassium, anhydrous citric acid, lemon flavor, polysorbate 80, povidone k-30, simethicone, sodium benzoate, sodium bicarbonate, sucralose, water

Questions or comments?

+1-866-359-3478 (M-F) 9 AM to 5 PM EST or www.pharmadel.com

Dist. by:

Pharmadel LLC.

New Castle, DE 19720